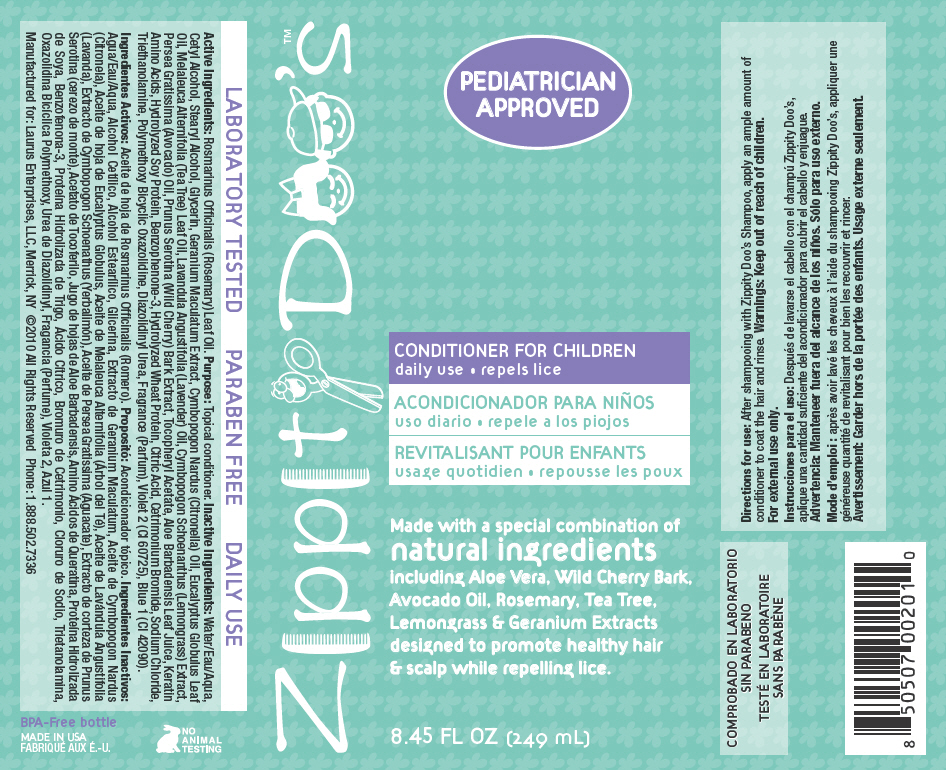 DRUG LABEL: Zippity Doos 
NDC: 57240-2010 | Form: LIQUID
Manufacturer: Laurus Enterprises, LLC
Category: homeopathic | Type: HUMAN OTC DRUG LABEL
Date: 20130228

ACTIVE INGREDIENTS: Rosemary Oil 2.49 mg/1 mL
INACTIVE INGREDIENTS: Water; Cetyl Alcohol; Stearyl Alcohol; Glycerin; Geranium Maculatum Root; Citronella Oil; Eucalyptus Oil; Tea Tree Oil; Lavender Oil; Avocado Oil; Prunus Serotina Bark; .Alpha.-Tocopherol Acetate; Aloe Vera Leaf; Oxybenzone; Citric Acid Monohydrate; Cetrimonium Bromide; Sodium Chloride; Trolamine; Diazolidinyl Urea; D&C Violet No. 2; FD&C Blue No. 1

Zippity Doo's™
CONDITIONER FOR CHILDREN

Active Ingredients

Rosmarinus Officinalis (Rosemary) Leaf Oil.

Purpose

Topical conditioner.

Inactive Ingredients

Water/Eau/Aqua, Cetyl Alcohol, Stearyl Alcohol, Glycerin, Geranium Maculatum Extract, Cymbopogon Nardus (Citronella) Oil, Eucalyptus Globulus Leaf Oil, Melaleuca Alternifolia (Tea Tree) Leaf Oil, Lavandula Angustifolia (Lavender) Oil, Cymbopogon Schoenanthus (Lemongrass) Extract, Persea Gratissima (Avocado) Oil, Prunus Serotina (Wild Cherry) Bark Extract, Tocopheryl Acetate, Aloe Barbadensis Leaf Juice, Keratin Amino Acids, Hydrolyzed Soy Protein, Benzophenone-3, Hydrolyzed Wheat Protein, Citric Acid, Cetrimonium Bromide, Sodium Chloride, Triethanolamine, Polymethoxy Bicyclic Oxazolidine, Diazolidinyl Urea, Fragrance (Parfum), Violet 2 (CI 60725), Blue 1 (CI 42090).

Directions for use

INDICATIONS AND USAGE

After shampooing with Zippity Doo's Shampoo, apply an ample amount of conditioner to coat the hair and rinse.

Warnings

Keep out of reach of children.

For external use only.

PRINCIPAL DISPLAY PANEL - 249 mL Bottle Label

Zippity Doo's™

PEDIATRICIAN
APPROVED

CONDITIONER FOR CHILDREN
daily use • repels lice

Made with a special combination of
natural ingredients
including Aloe Vera, Wild Cherry Bark,
Avocado Oil, Rosemary, Tea Tree,
Lemongrass & Geranium Extracts
designed to promote healthy hair
& scalp while repelling lice.

8.45 FL OZ (249 mL)